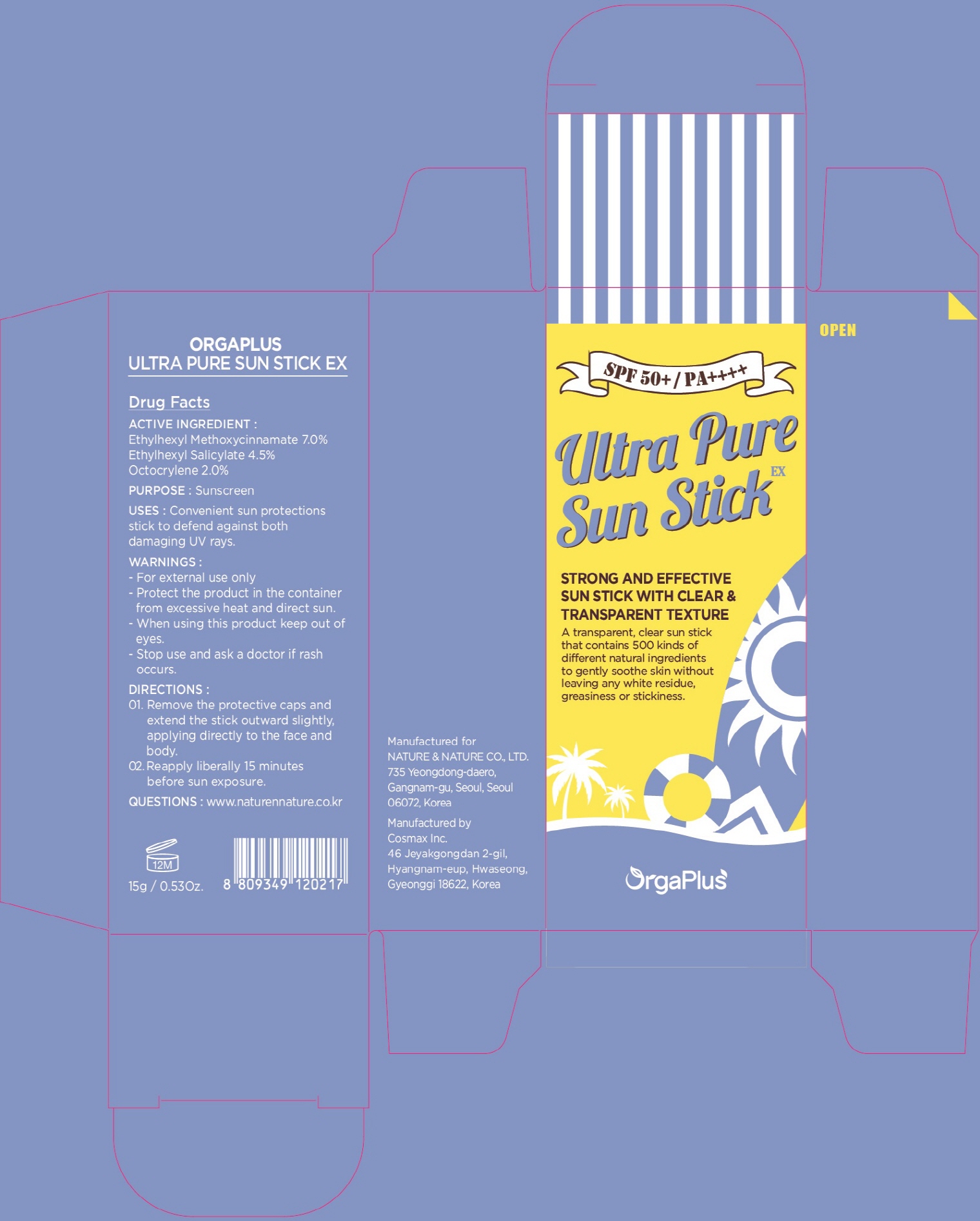 DRUG LABEL: OrgaPlus Ultra Pure Sun EX
NDC: 69777-240 | Form: STICK
Manufacturer: BLUEZONWIDE CO.,LTD
Category: otc | Type: HUMAN OTC DRUG LABEL
Date: 20250205

ACTIVE INGREDIENTS: OCTINOXATE 1.05 g/15 g; OCTISALATE 0.67 g/15 g; OCTOCRYLENE 0.3 g/15 g
INACTIVE INGREDIENTS: BUTYLENE GLYCOL

ACTIVE INGREDIENT

Active ingredients: Ethylhexyl Methoxycinnamate 7.0%, Ethylhexyl Salicylate 4.5%, Octocrylene 2.0%

INACTIVE INGREDIENT

Inactive ingredients:

Butylene Glycol Dicaprylate/Dicaprate, Polyamide-3, Polyamide-8, Octyldodecanol, Diethylamino Hydroxybenzoyl Hexyl Benzoate, Bis-Ethylhexyloxyphenol Methoxyphenyl Triazine, Dibutyl Lauroyl Glutamide, Dibutyl Ethylhexanoyl Glutamide, Citrus Aurantium Dulcis (Orange) Peel Oil, Chamaecyparis Obtusa Water, Gardenia Florida Fruit Extract, Persea Gratissima (Avocado) Oil, Brassica Oleracea Capitata (Cabbage) Leaf Extract, Daucus Carota Sativa (Carrot) Root Water, Solanum Lycopersicum (Tomato) Fruit Water, Solanum Tuberosum (Potato) Pulp Extract, Apium Graveolens (Celery) Extract, Brassica Oleracea Gongylodes Extract, Brassica Oleracea Italica (Broccoli) Water, Capsicum Annuum Fruit Extract, Cichorium Intybus (Chicory) Leaf Extract, Brassica Campestris (Rapeseed) Extract, Argania Spinosa Kernel Oil, Avena Sativa (Oat) Kernel Oil, Bertholletia Excelsa Seed Oil, Borago Officinalis Seed Oil, Citrus Aurantium Dulcis (Orange) Fruit Water, Oenothera Biennis (Evening Primrose) Oil, Olea Europaea (Olive) Fruit Oil, Plukenetia Volubilis Seed Oil, Prunus Amygdalus Dulcis (Sweet Almond) Oil, Raspberry Seed Oil/Tocopheryl Succinate Aminopropanediol Esters, Rosmarinus Officinalis (Rosemary) Leaf Oil, Simmondsia Chinensis (Jojoba) Seed Oil, Vitis Vinifera (Grape) Seed Oil, Anthemis Nobilis Flower Water, Rosmarinus Officinalis (Rosemary) Leaf Water, Calendula Officinalis Flower Water, Helianthus Annuus (Sunflower) Seed Oil, Hydrolyzed Hibiscus Esculentus Extract, Paeonia Lactiflora Extract, Centella Asiatica Extract, Calendula Officinalis Flower Extract, Nymphaea Alba Flower Extract, Borago Officinalis Extract, Hippophae Rhamnoides Fruit Extract, Centaurea Cyanus Flower Extract, Chamomilla Recutita (Matricaria) Flower/Leaf Extract, Hyacinthus Orientalis (Hyacinth) Extract, Lavandula Angustifolia (Lavender) Flower Water, Limonia Acidissima Extract, Salvia Sclarea (Clary) Extract, Xylitol, Epilobium Fleischeri Extract, Aloe Barbadensis Leaf Extract, Yeast Extract, Veronica Officinalis Extract, Alchemilla Vulgaris Extract, Melissa Officinalis Leaf Extract, Achillea Millefolium Extract, Malva Sylvestris (Mallow) Extract, Mentha Piperita (Peppermint) Leaf Extract, Primula Veris Extract, Hydrolyzed Viola Tricolor Extract, Artemisia Umbelliformis Extract, Buddleja Davidii Extract, Marrubium Vulgare Extract, Thymus Vulgaris (Thyme) Extract, Scutellaria Alpina Flower/Leaf/Stem Extract, Vanilla Tahitensis Fruit Extract, Cinnamomum Zeylanicum Bark Extract, Leontopodium Alpinum Flower/Leaf Extract, Rubus Chamaemorus Seed Extract, Tillandsia Usneoides Extract, Poterium Officinale Root Extract, Rosa Damascena Flower Extract, Anthemis Nobilis Flower Extract, Carthamus Tinctorius (Safflower) Flower Extract, Coix Lacryma-Jobi Ma-yuen Seed Extract, Nelumbo Nucifera Flower Extract, Origanum Vulgare Leaf Extract, Asparagus Cochinchinensis Root Extract, Portulaca Oleracea Extract, Chamaecyparis Obtusa Leaf Extract, Diospyros Kaki Leaf Extract, Ophiopogon Japonicus Root Extract, Panax Ginseng Root Extract, Prunus Persica (Peach) Kernel Extract, Astragalus Membranaceus Root Extract, Cassia Obtusifolia Seed Extract, Juglans Regia (Walnut) Seed Extract, Prunus Armeniaca (Apricot) Kernel Extract, Rehmannia Glutinosa Root Extract, Salix Alba (Willow) Bark Extract, Scutellaria Baicalensis Root Extract, Chrysanthemum Indicum Flower Extract, Lonicera Japonica (Honeysuckle) Flower Extract, Saussurea Involucrata Extract, Lithospermum Erythrorhizon Root Extract, Salvia Officinalis (Sage) Leaf Extract, Bellis Perennis (Daisy) Flower Extract, Camellia Japonica Flower Extract, Camellia Sinensis Flower Extract, Chrysanthemum Sinense Flower Extract, Citrus Aurantium Amara (Bitter Orange) Flower Extract, Lavandula Angustifolia (Lavender) Flower Extract, Achillea Millefolium Flower Extract, Arnica Montana Flower Extract, Dianthus Chinensis Extract, Gardenia Florida Flower Extract, Helianthus Annuus (Sunflower) Flower Extract, Hibiscus Sabdariffa Flower Extract, Jasminum Officinale (Jasmine) Flower Extract, Lonicera Caprifolium (Honeysuckle) Flower Extract, Prunus Serrulata Flower Extract, Punica Granatum Flower Extract, Rosa Centifolia Flower Extract, Rosa Gallica Flower Extract, Rosa Rugosa Flower Extract, Sambucus Nigra Flower Extract, Viola Mandshurica Flower Extract, Glycyrrhiza Glabra (Licorice) Root Extract, Pueraria Lobata Root Extract, Trichosanthes Kirilowii Root Extract, Aesculus Hippocastanum (Horse Chestnut) Seed Extract, Aspalathus Linearis Leaf Extract, Benincasa Cerifera Seed Extract, Bertholletia Excelsa Seed Extract, Camellia Japonica seed Extract, Camellia Sinensis Seed Extract, Canavalia Gladiata Seed Extract, Chenopodium Quinoa Seed Extract, Cinnamomum Cassia Bark Extract, Coffea Arabica (Coffee) Seed Extract, Corylus Avellana (Hazelnut) Seed Extract, Cucumis Sativus (Cucumber) Seed Extract, Cucurbita Pepo (Pumpkin) Seed Extract, Cuminum Cyminum (Cumin) Seed Extract, Morus Alba Bark Extract, Raphanus Sativus (Radish) Seed Extract, Rhus Semialata Gall Extract, Vitis Vinifera (Grape) Fruit Extract, Spirulina Platensis Extract, Angelica Gigas Root Extract, Chaenomeles Sinensis Fruit Extract, Cnidium Officinale Root Extract, Dioscorea Japonica Root Extract, Schisandra Chinensis Fruit Extract, Coptis Japonica Root Extract, Linum Usitatissimum (Linseed) Seed Extract, Alpinia Officinarum Root Extract, Arctium Lappa Root Extract, Artemisia Princeps Leaf Extract, Bupleurum Falcatum Root Extract, Chrysanthemum Zawadskii Extract, Dictamnus Dasycarpus Root Extract, Eriobotrya Japonica Leaf Extract, Glycine Soja (Soybean) Seed Extract, Houttuynia Cordata Extract, Imperata Cylindrica Root Extract, Juniperus Communis Fruit Extract, Lippia Citriodora Leaf Extract, Lycium Chinense Fruit Extract, Nigella Sativa Seed Extract, Paeonia Albiflora Root Extract, Perilla Frutescens Leaf Extract, Phellodendron Amurense Bark Extract, Platycodon Grandiflorum Root Extract, Polygonum Cuspidatum Root Extract, Poncirus Trifoliata Fruit Extract, Rosmarinus Officinalis (Rosemary) Leaf Extract, Salvia Hispanica Seed Extract, Sophora Japonica Bud Extract, Xanthium Strumarium Fruit Extract, Zingiber Officinale (Ginger) Root Extract, Achyranthes Japonica Extract, Acorus Gramineus Root/Stem Extract, Aesculus Hippocastanum (Horse Chestnut) Bark Extract, Althaea Officinalis Leaf Extract, Amaranthus Hypochondriacus Seed Extract, Anemarrhena Asphodeloides Root Extract, Angelica Acutiloba Root Extract, Angelica Dahurica Root Extract, Asarum Heterotropoides Rhizome Extract, Avena Sativa (Oat) Kernel Extract, Brassica Oleracea Italica (Broccoli) Extract, Carica Papaya (Papaya) Fruit Extract, Castanea Crenata (Chestnut) Shell Extract, Cichorium Intybus (Chicory) Flower Extract , Cimicifuga Simplex Root Extract, Citrullus Lanatus (Watermelon) Fruit Extract, Citrus Aurantium Dulcis (Orange) Fruit Extract, Citrus Limon (Lemon) Fruit Extract, Citrus Paradisi (Grapefruit) Fruit Extract, Citrus Unshiu Peel Extract, Cryptomeria Japonica Leaf Extract, Cuscuta Japonica Seed Extract, Cymbopogon Schoenanthus Extract, Dryopteris Crassirhizoma Root Extract, Echinacea Purpurea Extract, Eclipta Prostrata Extract, Elettaria Cardamomum Seed Extract, Ficus Carica (Fig) Fruit Extract, Foeniculum Vulgare (Fennel) Seed Extract, Fomes Fomentarius Extract, Fragaria Ananassa (Strawberry) Fruit Extract, Freesia Alba Flower Extract, Gastrodia Elata Root Extract, Glycine Soja (Soybean) Sprout Extract, Gossypium Herbaceum (Cotton) Seed Extract, Helianthus Annuus (Sunflower) Seed Extract, Hordeum Vulgare Seed Extract, Ilex Cornuta Extract, Impatiens Balsamina Flower Extract, Ipomoea Batatas Leaf Extract, Ipomoea Hederacea Seed Extract, Lactobacillus/Soybean Ferment Extract, Lavandula Angustifolia (Lavender) Extract, Lespedeza Cuneata Extract, Ligularia Fishceri Leaf Extract, Lupinus Albus Seed Extract, Lycium Chinense Flower Extract , Magnolia Obovata Bark Extract, Malva Sylvestris (Mallow) Leaf Extract, Mentha Arvensis Leaf Extract, Moringa Oleifera Seed Extract, Oenothera Biennis (Evening Primrose) Seed Extract, Origanum Majorana Leaf Extract, Paeonia Suffruticosa Bark Extract, Panicum Miliaceum (Millet) Seed Extract, Passiflora Incarnata Extract, Phaseolus Radiatus Seed Extract, Phaseolus Vulgaris (Kidney Bean) Seed Extract, Pinus Densiflora Root Extract, Pinus Koraiensis Seed Extract, Plantago Asiatica Seed Extract, Polygonatum Odoratum Extract, Polygonum Multiflorum Root Extract, Poria Cocos Extract, Prunus Amygdalus Dulcis (Sweet Almond) Seed Extract, Prunus Armeniaca (Apricot) Fruit Extract, Pyrus Pyrifolia (Pear) Fruit Extract, Quercus Serrata Extract, Red Ginseng Water(ICID미등재), Rhus Javanica Extract, Robinia Pseudoacacia Flower Extract, Rosa Canina Seed Extract, Rosa Davurica Bud Extract, Rosmarinus Officinalis (Rosemary) Extract, Rubia Cordifolia Root Extract, Saponaria Officinalis Leaf/Root Extract, Saposhnikovia Divaricata Root Extract, Sasa Quelpaertensis Extract, Schizonepeta Tenuifolia Extract, Secale Cereale (Rye) Seed Extract, Sesamum Indicum (Sesame) Seed Extract, Sigesbeckia Orientalis Extract, Simmondsia Chinensis (Jojoba) Seed Extract, Solanum Lycopersicum (Tomato) Fruit Extract, Sophora Flavescens Root Extract, Sorbus Commixta Berry Extract, Tanacetum Cinerariifolium (Pyrethrum) Flower Extract, Taraxacum Platycarpum Extract, Torilis Japonica Extract, Triticum Vulgare (Wheat) Seed Extract, Vitis Vinifera (Grape) Seed Extract, Ziziphus Jujuba Fruit Extract, Dictyopteris Membranacea Extract, Porphyra Tenera Extract, Laurus Nobilis Leaf Extract, Prunus Mume Fruit Extract, Salicornia Herbacea Extract, Codonopsis Lanceolata Root Extract, Corthellus Shiitake (Mushroom) Extract, Eucalyptus Globulus Leaf Extract, Leonurus Sibiricus Flower/Leaf/Stem Extract, Morus Alba Fruit Extract, Triticum Vulgare (Wheat) Sprout Extract, Laminaria Digitata Extract, Laminaria Japonica Extract, Acanthopanax Senticosus (Eleuthero) Root Extract, Acorus Calamus Rhizome Water, Actinidia Chinensis (Kiwi) Fruit Extract, Actinidia Chinensis (Kiwi) Fruit Water, Aesculus Hippocastanum (Horse Chestnut) Extract, Agastache Rugosa Extract, Agrimonia Eupatoria Extract, Agrimonia Pilosa Extract, Alchemilla Vulgaris Leaf Extract, Allium Sativum (Garlic) Bulb Extract, Althaea Officinalis Root Extract, Annona Cherimola Fruit Extract, Aronia Melanocarpa Fruit Extract, Artemisia Princeps Leaf Water, Avena Sativa (Oat) Meal Extract, Bambusa Vulgaris Leaf Extract, Bambusa Vulgaris Water, Belamcanda Chinensis Root Extract, Betula Platyphylla Japonica Bark Extract, Black Strap Powder, Bletilla Striata Root Extract, Brassica Oleracea Acephala Leaf Extract, Brassica Oleracea Gemmifera (Brussels Sprouts) Extract, Brassica Oleracea Italica (Broccoli) Sprout Extract, Camellia Sinensis Leaf Water, Camellia Sinensis Leaf Water, Carica Papaya (Papaya) Fruit Water, Centaurea Cyanus Flower Water, Charcoal Powder, Chrysanthellum Indicum Flower Water, Chrysanthemum Boreale Flower Extract, Coffea Arabica (Coffee) Fruit Extract, Coix Lacryma-Jobi Ma-yuen Seed Water, Cordyceps Sinensis Extract, Crocus Sativus Flower Extract, Cucumis Melo (Melon) Fruit Water, Cucumis Sativus (Cucumber) Fruit Water, Daucus Carota Sativa (Carrot) Root Extract, Echinacea Angustifolia Extract, Echinacea Angustifolia Leaf Extract, Enteromorpha Compressa Extract, Epilobium Angustifolium Flower/Leaf/Stem Extract, Epimedium Koreanum Extract, Eucommia Ulmoides Bark Extract, Euterpe Oleracea Fruit Extract, Fagus Sylvatica Seed Extract, Foeniculum Vulgare (Fennel) Leaf Extract, Ganoderma Lucidum (Mushroom) Stem Extract, Gentiana Scabra Root Extract, Ginkgo Biloba Leaf Water, Glycine Soja (Soybean) Seed Extract, Glycyrrhiza Glabra (Licorice) Root Water, Helianthus Annuus (Sunflower) Sprout Extract, Hordeum Distichon (Barley) Extract, Hypericum Erectum Extract, Hyssopus Officinalis Extract, Ilex Paraguariensis Leaf Extract, Inonotus Obliquus (Mushroom) Extract, Inula Helenium Extract, Ipomoea Batatas Root Extract, Iris Ensata Extract, Iris Versicolor Extract, Lepidium Sativum Sprout Extract, Lilium Candidum Flower Extract, Lonicera Caprifolium (Honeysuckle) Extract, Luffa Cylindrica Fruit Extract, Magnolia Liliflora Bud Extract, Melissa Officinalis Flower/Leaf/Stem Water, Mentha Arvensis Extract, Mentha Viridis (Spearmint) Extract, Mirabilis Jalapa Seed Extract, Momordica Charantia Fruit Extract, Monarda Didyma Leaf Extract, Musa Sapientum (Banana) Water, Myosotis Sylvatica Flower/Leaf/Stem Extract, Nelumbo Nucifera Flower Water, Ocimum Basilicum (Basil) Leaf Extract, Olea Europaea (Olive) Fruit Extract, Origanum Vulgare Extract, Oryza Sativa (Rice) Extract, Oryza Sativa (Rice) Extract, Oryza Sativa (Rice) Seed Water, Paeonia Albiflora Flower Extract, Panax Ginseng Berry Extract, Pelargonium Graveolens Extract, Perilla Ocymoides Seed Extract, Persea Gratissima (Avocado) Fruit Extract, Peucedanum Graveolens (Dill) Extract, Phaseolus Angularis Seed Extract, Phaseolus Radiatus Sprout Extract, Physalis Alkekengi Fruit Extract, Pinus Sylvestris Bud Extract, Piper Nigrum (Pepper) Seed Extract, Pollen Extract, Polygala Tenuifolia Root Extract, Polygonum Fagopyrum (Buckwheat) Seed Extract, Portulaca Grandiflora Extract, Prunella Vulgaris Extract, Prunella Vulgaris Leaf Extract, Prunus Mume Flower Water, Prunus Mume Fruit Water, Prunus Persica (Peach) Flower Extract, Rosa Canina Flower Extract, Rose Extract, Royal Jelly Extract, Rubus Coreanus Fruit Extract, Salvia Officinalis (Sage) Extract, Salvia Officinalis (Sage) Leaf Water, Salvia Officinalis (Sage) Water, Sambucus Nigra Fruit Extract, Saponaria Officinalis Extract, Saponaria Officinalis Root Extract, Scrophularia Buergeriana Extract, Sesamum Indicum (Sesame) Sprout Extract, Solanum Melongena (Eggplant) Fruit Extract, Sparassis Crispa Extract, Spinacia Oleracea (Spinach) Leaf Extract, Stevia Rebaudiana Extract, Thamnolia Vermicularis Leaf Extract, Theobroma Cacao (Cocoa) Extract, Tricholoma Matsutake Extract, Tropaeolum Majus Flower Extract, Ulmus Davidiana Root Extract, Vaccinium Angustifolium (Blueberry) Fruit Extract, Verbena Officinalis Extract, Vitis Vinifera (Grape) Fruit Water, Wasabia Japonica Root Extract, Zea Mays (Corn) Silk Extract, Zingiber Officinale (Ginger) Water, Laminaria Japonica Extract, Alaria Esculenta Extract, Ascophyllum Nodosum Extract, Capsosiphon Fulvescens Extract, Caulerpa Lentillifera Extract, Chlorella Vulgaris Extract, Chondrus Crispus Extract, Cladosiphon Okamuranus Extract, Codium Fragile Extract, Ecklonia Cava Extract, Fucus Vesiculosus Extract, Gelidium Cartilagineum Extract, Gracilaria Verrucosa Extract, Hizikia Fusiforme Extract, Jania Rubens Extract, Laminaria Hyperborea Extract, Laminaria Saccharina Extract, Macrocystis Pyrifera (Kelp) Extract, Nereocystis Leutkeana Extract, Padina Pavonica Thallus Extract, Palmaria Palmata Extract, Plankton Extract, Porphyra Yezoensis Extract, Sargassum Fulvellum Extract, Sea Whip Extract, Solidago Virgaurea (Goldenrod) Extract, Undaria Pinnatifida Extract, Acorus Calamus Root Extract, Atractylodes Japonica Rhizome Extract, Cornus Officinalis Fruit Extract, Forsythia Suspensa Fruit Extract, Angelica Archangelica Root Extract, Argania Spinosa Kernel Extract, Averrhoa Carambola Fruit Extract, Camellia Sinensis Leaf Extract, Chrysanthellum Indicum Extract, Citrus Aurantium Dulcis (Orange) Flower Extract, Citrus Junos Fruit Extract, Cocos Nucifera (Coconut) Fruit Extract, Cucumis Sativus (Cucumber) Fruit Extract, Garcinia Mangostana Peel Extract, Ginkgo Biloba Leaf Extract, Hamamelis Virginiana (Witch Hazel) Leaf Extract, Hibiscus Esculentus Fruit Extract, Hippophae Rhamnoides Extract, Honey Extract, Hydrolyzed Coral, Lepidium Meyenii Root Extract, Lilium Tigrinum Extract, Magnolia Liliflora Flower Extract, Malt Extract, Mangifera Indica (Mango) Fruit Extract, Morus Alba Leaf Extract, Musa Sapientum (Banana) Fruit Extract, Oryza Sativa (Rice) Bran Extract, Paeonia Lactiflora Root Extract, Panax Ginseng Root Extract, Passiflora Edulis Fruit Extract, Phellinus Linteus Extract, Pinus Palustris Leaf Extract, Plumeria Rubra Flower Extract, Prunus Domestica Fruit Extract, Psidium Guajava Fruit Extract, Punica Granatum Extract, Rubus Fruticosus (Blackberry) Fruit Extract, Scabiosa Arvensis Extract, Swiftlet Nest Extract, Uncaria Tomentosa Extract, Althaea Rosea Flower Extract, Angelica Keiskei Extract, Aspalathus Linearis Extract, Bambusa Vulgaris Extract, Cassia Tora Seed Extract, Chamomilla Recutita (Matricaria) Extract, Corydalis Turtschaninovii Root Extract, Cucurbita Pepo (Pumpkin) Fruit Extract, Curcuma Longa (Turmeric) Root Extract, Cuscuta Australis Seed Extract, Cymbopogon Citratus Extract, Diospyros Kaki Fruit Extract, Equisetum Arvense Extract, Eucommia Ulmoides Leaf Extract, Ganoderma Lucidum (Mushroom) Extract, Gynostemma Pentaphyllum Leaf/Stem Extract, Hovenia Dulcis Fruit Extract, Hydrolyzed Pearl, Leontopodium Alpinum Extract, Macadamia Ternifolia Seed Extract, Magnolia Kobus Bark Extract, Melissa Officinalis Extract, Mentha Rotundifolia Leaf Extract, Morus Alba Root Extract, Nelumbo Nucifera Seed Extract, Oenothera Biennis (Evening Primrose) Flower Extract, Paeonia Suffruticosa Root Extract, Phyllanthus Emblica Fruit Extract, Pinus Densiflora Leaf Extract, Plantago Asiatica Extract, Polygonatum Officinale Rhizome/Root Extract, Prunus Mume Flower Extract, Punica Granatum Fruit Extract, Pyrus Malus (Apple) Fruit Extract, Rehmannia Chinensis Root Extract, Rosa Canina Fruit Extract, Rosa Damascena Extract, Rubus Idaeus (Raspberry) Fruit Extract, Sapindus Mukorossi Fruit Extract, Selaginella Tamariscina Extract, Thuja Orientalis Extract, Trametes Versicolor Extract, Tremella Fuciformis (Mushroom) Extract, Uncaria Gambir Extract, Glycerin, Pentaerythrityl Tetra-di-t-butyl Hydroxyhydrocinnamate, Butylene Glycol, Water, 1,2-Hexanediol, Hexylene Glycol, Dipropylene Glycol, Dextrin, Xylitylglucoside, Aqua(EU), Anhydroxylitol, Sodium Palmitoyl Proline, Capryloyl Glycine, Caprylic/Capric Triglyceride, Dipotassium Phosphate, Ethylhexylglycerin, Acetyl Glutamine, Hydrogenated Lecithin, Cassia Angustifolia Seed Polysaccharide, Citric Acid, Ceramide NP, Sarcosine, Ethyl Hexanediol, Caprylyl Glycol, Cellulose Gum, Sepia Extract (EU), Lactic Acid, Phenoxyethanol, Sodium Benzoate, Potassium Sorbate, Benzyl Alcohol, Dehydroacetic Acid

PURPOSE

Purpose: Sunscreen

WARNINGS

-For external use only

-Protect the product in the container from excessive heat and direct sun.

-When using this product keep out of eyes.

-Stop use and ask a doctor if rash occurs.

Uses:

Convenient sun protections stick to defend against both damaging UV rays.

Keep out of reach of children

Directions:
01. Remove the protective caps and extend the stick outward slightly, applying directly to the face and body.
02. Reapply liberally 15 minutes before sun exposure.